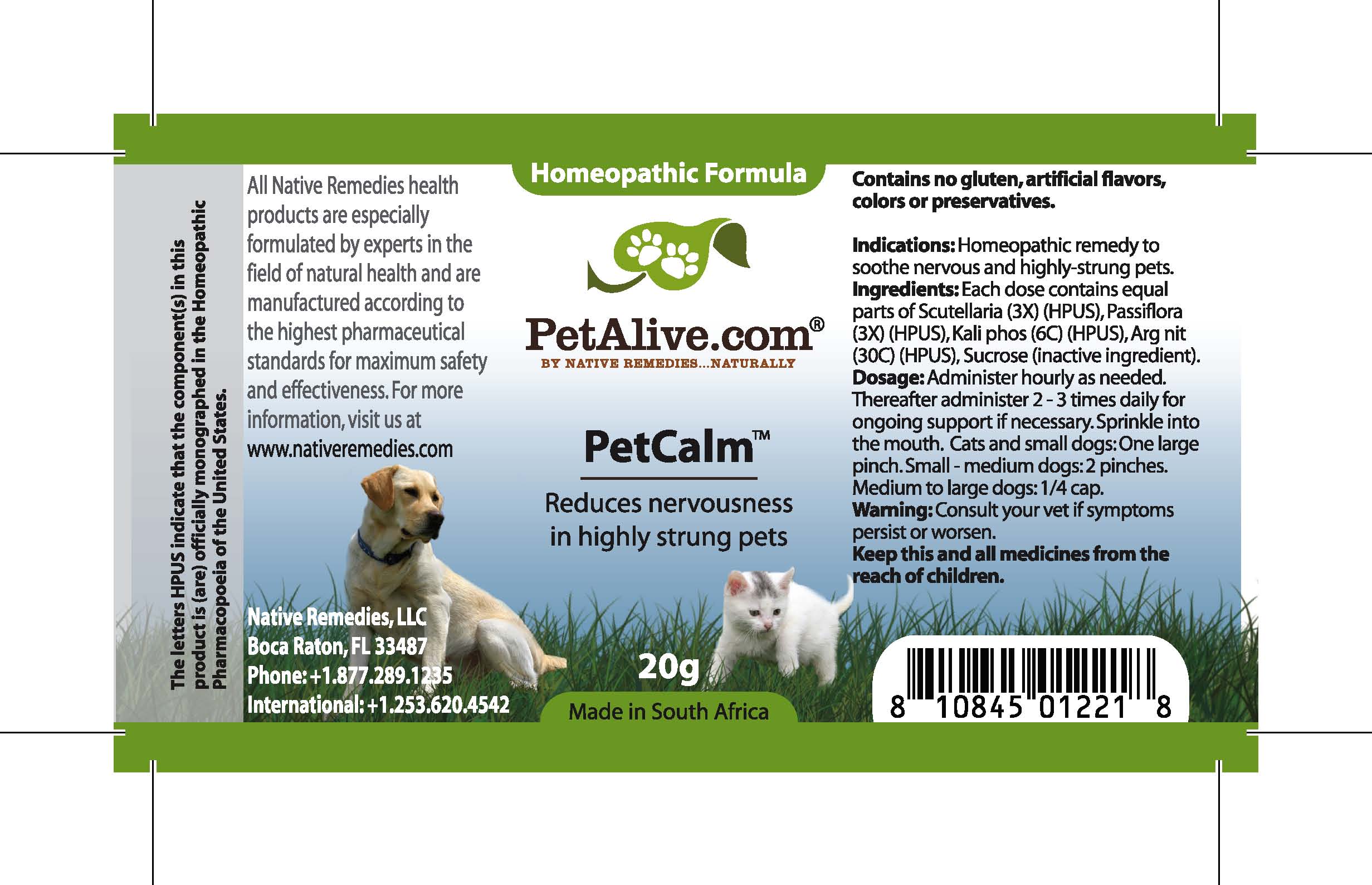 DRUG LABEL: PetCalm
NDC: 68647-155 | Form: GRANULE
Manufacturer: Feelgood Health
Category: homeopathic | Type: OTC ANIMAL DRUG LABEL
Date: 20100906

ACTIVE INGREDIENTS: SCUTELLARIA LATERIFLORA 3 [hp_X]/50 mg; PASSIFLORA INCARNATA TOP 3 [hp_X]/50 mg; POTASSIUM PHOSPHATE, DIBASIC 6 [hp_C]/50 mg; SILVER NITRATE 30 [hp_C]/50 mg
INACTIVE INGREDIENTS: SUCROSE 20000 mg/20000 mg

PETCALM

PURPOSE

Reduces nervousness in highly strung pets

INDICATIONS AND USAGE

Indications: Homeopathic remedy to soothe nervous and highly-strung pets.

DOSAGE AND ADMINISTRATION

Dosage: Administer hourly as needed. Thereafter administer 2-3 times daily for ongoing support if necessary. Sprinkle into the mouth.Cats and dogs under 20 lbs: 1 large pinch. Dogs 20-50 lbs: 2 pinches. Dogs over 50 lbs:1/4 cap.

GENERAL PRECAUTIONS

Caution: Consult your vet if symptoms persist or worsen.

ACTIVE INGREDIENT

Ingredients: Each dose contains equal parts of Scutellaria (3X) (HPUS), Passiflora (3X) (HPUS), Kali phos (6C) (HPUS), Arg nit (30C) (HPUS).

Sucrose (inactive ingredient).

WARNINGS

Contains no gluten, artificial flavors, colors or preservatives.

PATIENT COUNSELING INFORMATION

All Native Remedies health products are especially formulated by experts in the field of natural health and are manufactured according to the highest pharmaceutical standards for maximum safety and effectiveness. For more information, visit us at www.petalive.com

Distributed by

Native Remedies, LLC

6531 Park of Commerce Blvd.

Suite 160

Boca Raton, FL 33487

Phone: 1.877.289.1235

International: + 1.561.999.8857

The letters HPUS indicate that the component(s) in this product is (are) officially monographed in the Homeopathic Pharmacopoeia of the United States.

KEEP OUT OF REACH OF CHILDREN

Keep this and all medicines from the reach of children.